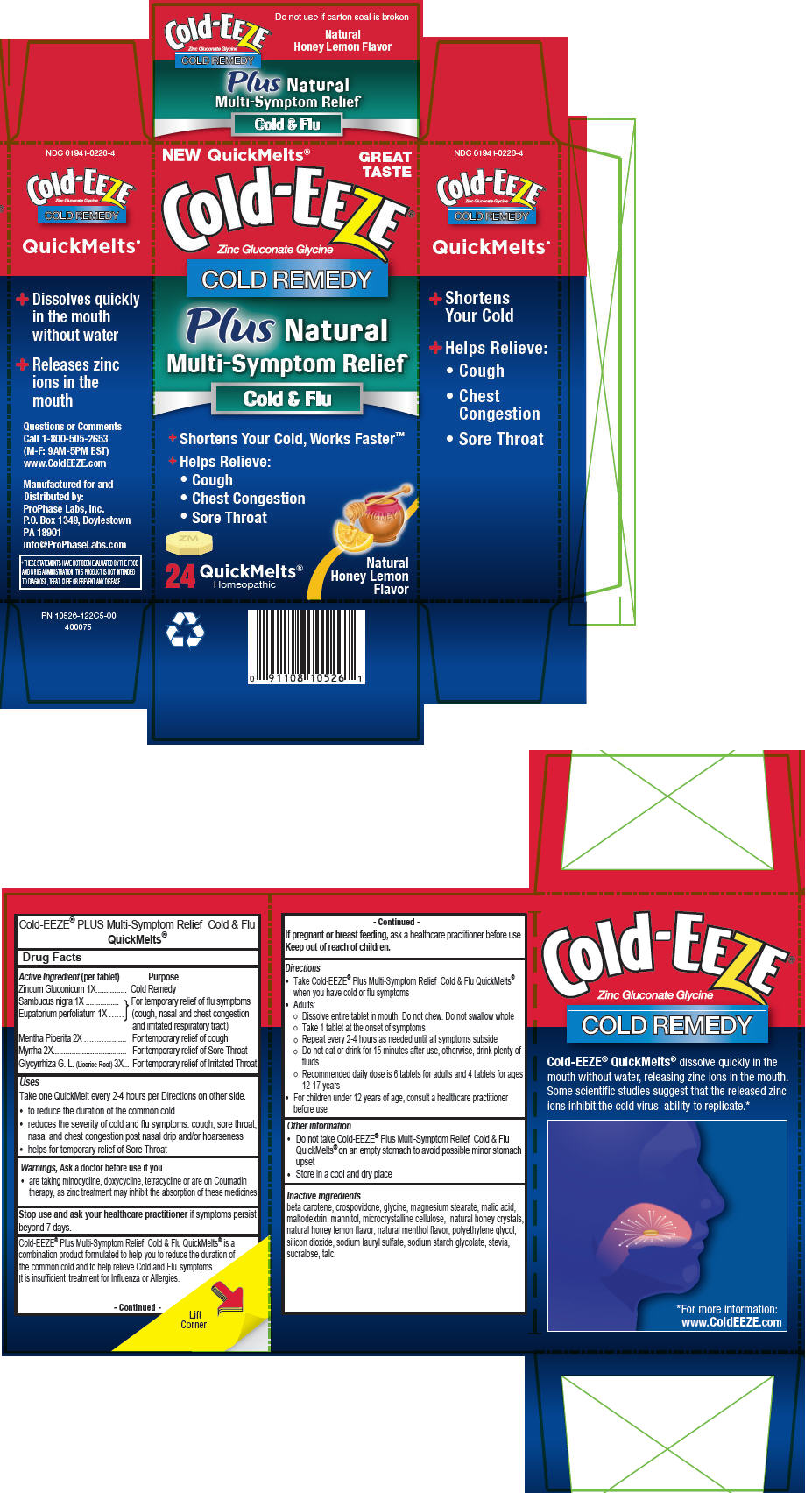 DRUG LABEL: Cold-EEZE 
NDC: 61941-0226 | Form: TABLET, ORALLY DISINTEGRATING
Manufacturer: ProPhase Labs, Inc.
Category: homeopathic | Type: HUMAN OTC DRUG LABEL
Date: 20141124

ACTIVE INGREDIENTS: Zinc Gluconate 1 [hp_X]/1 1; Sambucus Nigra Flower 1 [hp_X]/1 1; Eupatorium Perfoliatum Flowering Top 1 [hp_X]/1 1; Mentha Piperita 2 [hp_X]/1 1; Myrrh 2 [hp_X]/1 1; Glycyrrhiza Glabra Leaf 3 [hp_X]/1 1
INACTIVE INGREDIENTS: Glycine; .Beta.-Carotene; Crospovidone; MAGNESIUM STEARATE; MALIC ACID; MALTODEXTRIN; MANNITOL; CELLULOSE, MICROCRYSTALLINE; Honey; POLYETHYLENE GLYCOLS; SILICON DIOXIDE; SODIUM LAURYL SULFATE; SODIUM STARCH GLYCOLATE TYPE A POTATO; STEVIA REBAUDIUNA LEAF; SUCRALOSE; TALC

Cold-EEZE®
Natural Multi-Symptom Relief

Drug Facts

ACTIVE INGREDIENT

Active Ingredient (per tablet) | Purpose
Zincum Gluconicum 1X | Cold Remedy
Sambucus nigra 1X Eupatorium perfoliatum 1X | For temporary relief of flu symptoms (cough, nasal and chest congestion and irritated respiratory tract)
Mentha Piperita 2X | For temporary relief of cough
Myrrha 2X | For temporary relief of Sore Throat
Glycyrrhiza G. L. (Licorice Root) 3X | For temporary relief of Irritated Throat

Uses

Take one QuickMelt every 2-4 hours per Directions on other side.

- to reduce the duration of the common cold
- reduces the severity of cold and flu symptoms: cough, sore throat, nasal and chest congestion post nasal drip and/or hoarseness
- helps for temporary relief of Sore Throat

Warnings

Ask a doctor before use if you

- are taking minocycline, doxycycline, tetracycline or are on Coumadin therapy, as zinc treatment may inhibit the absorption of these medicines

Stop use and ask your healthcare practitioner if symptoms persist beyond 7 days.

Cold-EEZE® Plus Multi-Symptom Relief Cold & Flu QuickMelts® is a combination product formulated to help you to reduce the duration of the common cold and to help relieve Cold and Flu symptoms. It is insufficient treatment for Influenza or Allergies.

PREGNANCY OR BREAST FEEDING

If pregnant or breast feeding, ask a healthcare practitioner before use.

Keep out of reach of children.

Directions

- Take Cold-EEZE® Plus Multi-Symptom Relief Cold & Flu QuickMelts® when you have cold or flu symptoms
- Adults:
  - Dissolve entire tablet in mouth. Do not chew. Do not swallow whole
  - Take 1 tablet at the onset of symptoms
  - Repeat every 2-4 hours as needed until all symptoms subside
  - Do not eat or drink for 15 minutes after use, otherwise, drink plenty of fluids
  - Recommended daily dose is 6 tablets for adults and 4 tablets for ages 12-17 years
- For children under 12 years of age, consult a healthcare practitioner before use

Other information

- Do not take Cold-EEZE® Plus Multi-Symptom Relief Cold & Flu QuickMelts® on an empty stomach to avoid possible minor stomach upset
- Store in a cool and dry place

Inactive ingredients

beta carotene, crospovidone, glycine, magnesium stearate, malic acid, maltodextrin, mannitol, microcrystalline cellulose, natural honey crystals, natural honey lemon flavor, natural menthol flavor, polyethylene glycol, silicon dioxide, sodium lauryl sulfate, sodium starch glycolate, stevia, sucralose, talc.

Questions or Comments

Call 1-800-505-2653
(M-F: 9AM-5PM EST)

Manufactured for and
Distributed by:
ProPhase Labs, Inc.
P.O. Box 1349, Doylestown
PA 18901

PRINCIPAL DISPLAY PANEL - 24 Tablet Blister Pack Carton

NEW QuickMelts®

GREAT
TASTE

Cold-EEZE®

Zinc Gluconate Glycine

COLD REMEDY

Plus Natural
Multi-Symptom Relief

Cold & Flu

+ Shortens Your Cold, Works Faster™
+ Helps Relieve:
  - Cough
  - Chest Congestion
  - Sore Throat

24 QuickMelts®
Homeopathic

Natural
Honey Lemon
Flavor